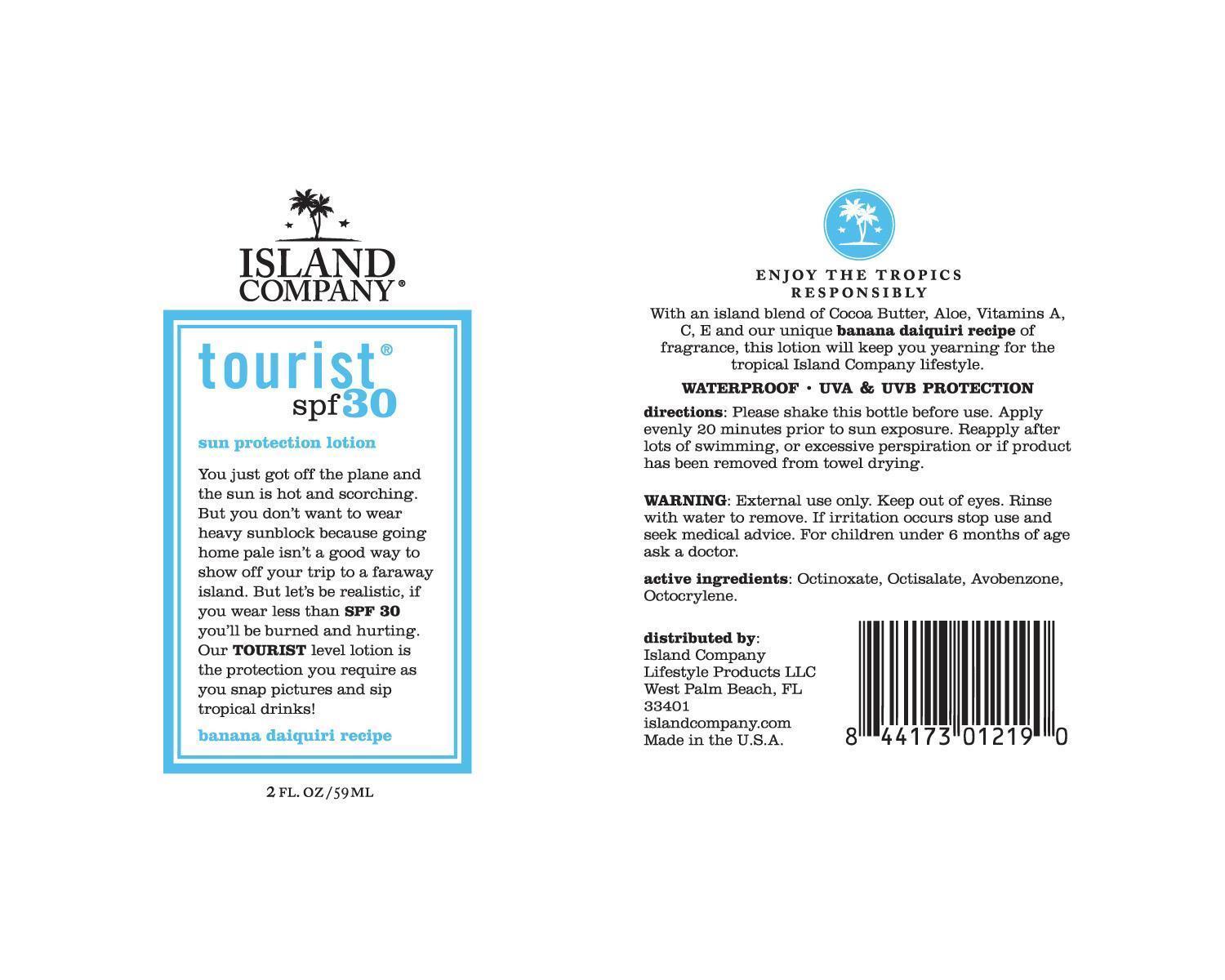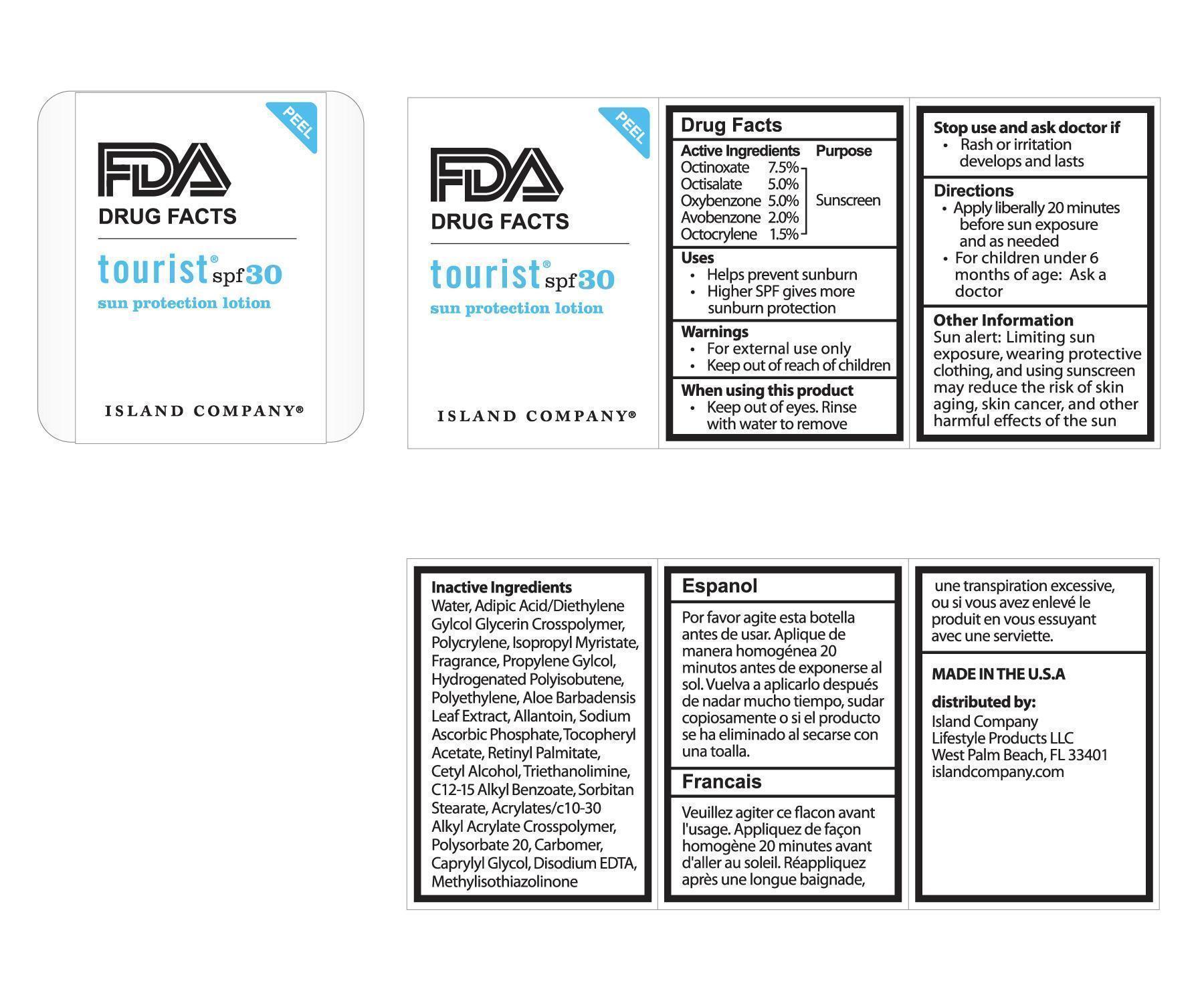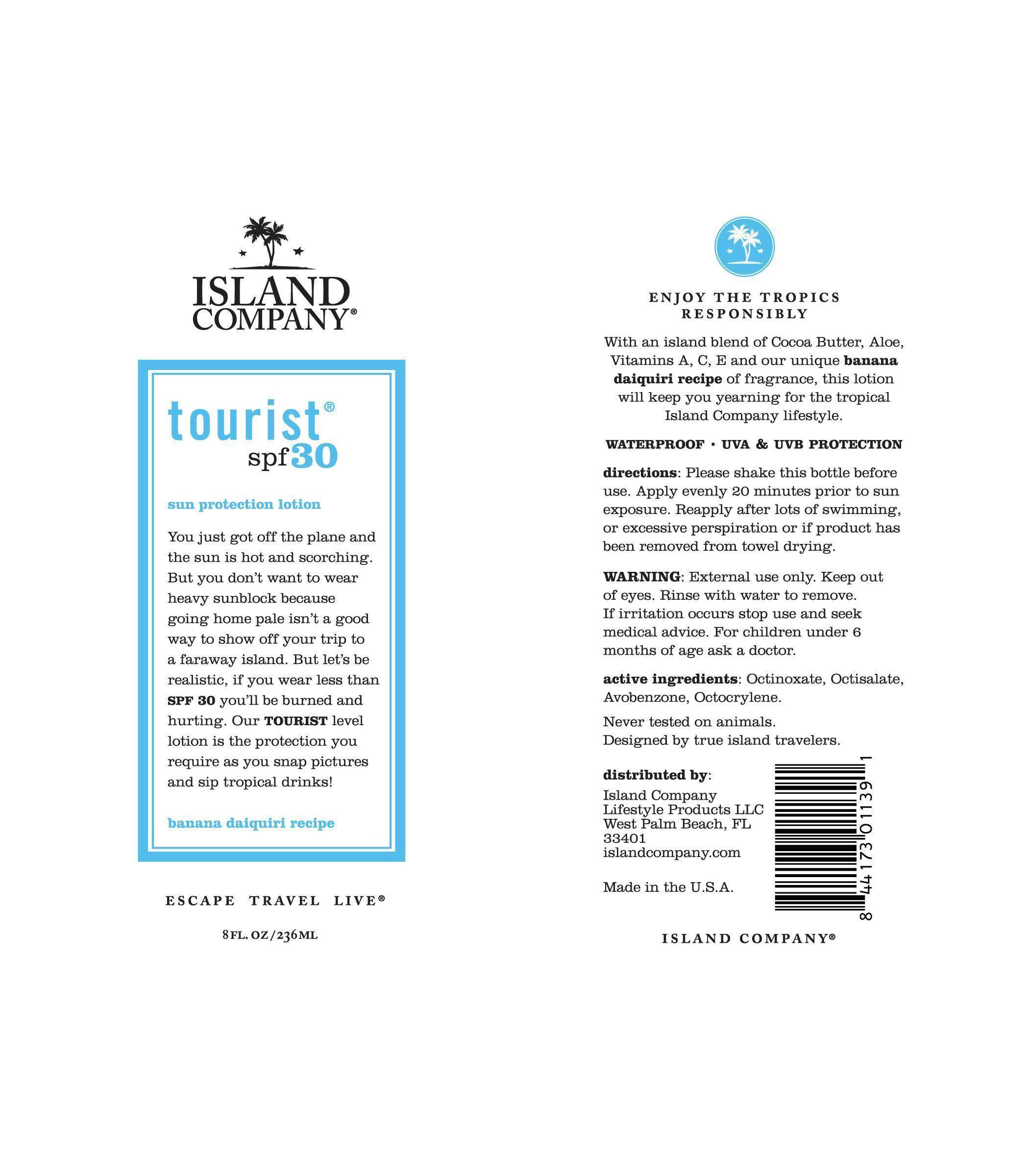 DRUG LABEL: tourist spf30
NDC: 10755-030 | Form: LOTION
Manufacturer: Island Company Lifestyle Products, LLC
Category: otc | Type: HUMAN OTC DRUG LABEL
Date: 20140414

ACTIVE INGREDIENTS: OCTINOXATE 75 mg/1 g; OCTISALATE 50 mg/1 g; AVOBENZONE 20 mg/1 g; OXYBENZONE 50 mg/1 g; OCTOCRYLENE 15 mg/1 g
INACTIVE INGREDIENTS: ADIPIC ACID; DIETHYLENE GLYCOL; GLYCERIN; C12-15 ALKYL BENZOATE; CARBOMER COPOLYMER TYPE A; TROLAMINE; DIPROPYLENE GLYCOL; CAPRYLYL GLYCOL; METHYLISOTHIAZOLINONE; PROPYLENE GLYCOL; ALOE VERA LEAF; ISOPROPYL MYRISTATE; POLYSORBATE 20; HIGH DENSITY POLYETHYLENE; CARBOMER INTERPOLYMER TYPE A (55000 CPS); EDETATE DISODIUM ANHYDROUS; ALLANTOIN; SODIUM ASCORBYL PHOSPHATE; HYDROGENATED POLYBUTENE (1300 MW); CETYL ALCOHOL; POLYESTER-8 (1400 MW, CYANODIPHENYLPROPENOYL CAPPED); .ALPHA.-TOCOPHEROL ACETATE, DL-; VITAMIN A PALMITATE; SORBITAN MONOSTEARATE

tourist spf30

Active Ingredients Purpose

Octinoxate 7.5% Sunscreen

Octisalate 5.0% Sunscreen

Oxybenzone 5.0% Sunscreen

Avobenzone 2.0% Sunscreen

Octocrylene 1.5% Sunscreen

Uses

- Helps prevent sunburn
- Higher SPF gives more sunburn protection

Warnings

- For external use only
- Keep out of reach of children

When using this product

- Keep out of eyes. Rinse with water to remove

Stop use and ask doctor if

- Rash or irritation develops and lasts

Directions

- Apply liberally 20 minutes before sun exposure and as needed
- For children under 6 months of age: Ask a doctor

Other Information

Sun alert: Limiting sun exposure, wearing protective clothing, and using sunscreen may reduce the risk of skin aging, skin cancer, and other harmful effects of the sun